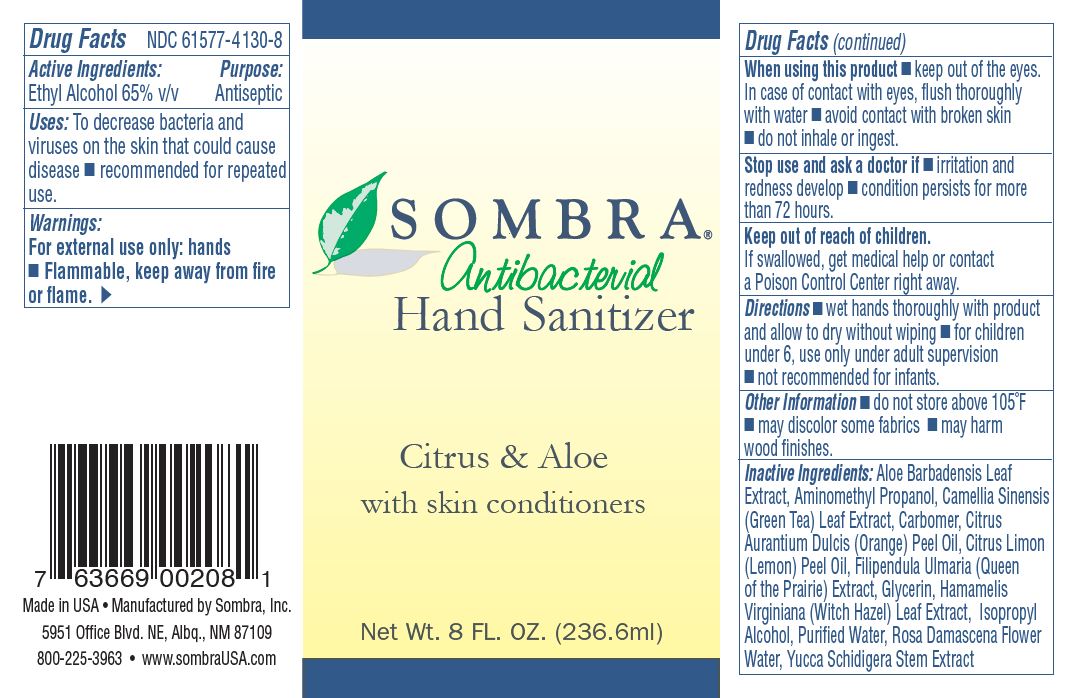 DRUG LABEL: SOMBRA ANTIBACTERIAL HAND SANITIZER
NDC: 61577-4130 | Form: GEL
Manufacturer: SOMBRA COSMETICS
Category: otc | Type: HUMAN OTC DRUG LABEL
Date: 20200729

ACTIVE INGREDIENTS: ALCOHOL 65 mL/100 mL
INACTIVE INGREDIENTS: WATER; GLYCERIN; ISOPROPYL ALCOHOL; LEMON PEEL; ORANGE OIL; AMINOMETHYLPROPANOL; ROSA DAMASCENA FLOWER; WITCH HAZEL; YUCCA SCHIDIGERA STEM; FILIPENDULA ULMARIA WHOLE; GREEN TEA LEAF; ALOE VERA LEAF

Sombra Antibacterial Hand Sanitizer

Active Ingredients

Ethyl Alcohol 65% v/v

Uses

To decrease bacteria and viruses on the skin that could cause disease. Recommended for repeated use.

Warnings

For external use only: hands. Flammable, keep away from fire or flame.

Do not use

avoid contact with broken skin. Do not inhale or ingest. Children under 6, use only
under adult supervision. Not recommended for infants.

When Using

When using this product, keep out of the eyes. In case of contact with eyes, flush thoroughly with water.

Stop use if irritation and redness develop or if condition persists for more than 72 hours.

KEEP OUT OF REACH OF CHILDREN

If swallowed, get medical help or contact a Poison Control Center right away.

Directions

Wet hands thoroughly with product and allow to dry without wiping.

Storage and Handling

Do not store above 105 F. May discolor some fabrics and may harm wood finishes.

Inactive ingredients

glycerin, purified water, isopropyl alcohol, aminomethyl propanol, citrus limon (lemon) peel oil, citrus aurantium dulcis (orange) peel oil, yucca schidigera stem extract, rosa damascena flower water, hamamelis virginiana (witch hazel) leaf extract, filipendula ulmaria (queen of the prairie) extract, camellia sinensis (green tea) leaf extract, aloe barbadensis leaf extract.

Purpose

Antiseptic